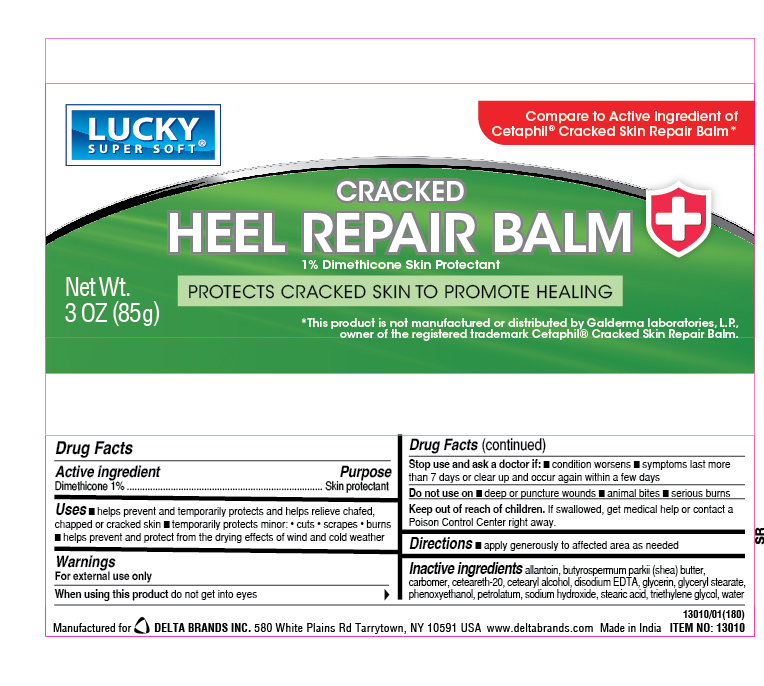 DRUG LABEL: Cracked Heel Repair Balm
NDC: 20276-042 | Form: CREAM
Manufacturer: Delta Brands Inc.
Category: otc | Type: HUMAN OTC DRUG LABEL
Date: 20260130

ACTIVE INGREDIENTS: DIMETHICONE 10 mg/1 g
INACTIVE INGREDIENTS: BUTYROSPERMUM PARKII (SHEA) BUTTER; CARBOMER; PHENOXYETHANOL; CETEARYL ALCOHOL; GLYCERIN; PETROLATUM; GLYCERYL STEARATE; ALLANTOIN; STEARIC ACID; TRIETHYLENE GLYCOL; WATER; SODIUM HYDROXIDE; CETEARETH-20; EDETATE DISODIUM

Cracked Heel Balm 1%Dimethicone

Active ingredient

Dimethicone 1%

Purpose

Skin protectant

Uses

■ helps prevent and temporarily protects and helps relieve chafed, chapped or cracked skin ■ temporarily protects minor: • cuts • scrapes • burns ■ helps prevent and protect from the drying effects of wind and cold weather

Warnings

For external use only

When using this product

do not get into eyes

Stop use and ask a doctor if:

■ conditon worsens ■ symptoms last more than 7 days or clear up and occur again wihtin a few days

Do not use on

■ deep or puncture wounds ■ animal bites ■ serious burns

Keep out of reach of children. If swallowed, get medical help or contact a Poison Control Center right away.

Directions

■ apply generously to affected area as needed

Inactive ingredients

allantoin, butyrospermum parkii (shea) butter, carbomer, ceteareth-20, cetearyl alcohol, disodium EDTA, glycerin, glyceryl stearate, phenoxyethanol, petrolatum, sodium hydroxide, stearic acid, triethylene glycol, water